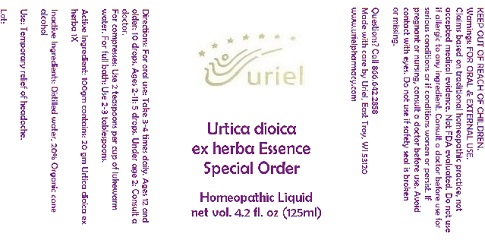 DRUG LABEL: Urtica dioica ex herba Essence Special Order
NDC: 48951-9189 | Form: LIQUID
Manufacturer: Uriel Pharmacy Inc.
Category: homeopathic | Type: HUMAN OTC DRUG LABEL
Date: 20180501

ACTIVE INGREDIENTS: URTICA DIOICA LEAF 1 [hp_X]/1 mL
INACTIVE INGREDIENTS: WATER; ALCOHOL

Urtica dioica ex herba Essence Special Order

INDICATIONS AND USAGE

Directions: For oral use: Take 3-4 times daily.

DOSAGE AND ADMINISTRATION

Take 3-4 times daily. Ages 12 and older: 10 drops. Ages 2-11: 5 drops. Under age 2: Consult a doctor.

Active Ingredient: 100gm contains: 20 gm Urtica dioica ex herba 1X

Inactive Ingredients: Distilled water, 20% Organic cane alcohol

PURPOSE

Use: Temporary relief of headache.

KEEP OUT OF REACH OF CHILDREN.

Warnings: FOR ORAL & EXTERNAL USE.
Claims based on traditional homeopathic practice, not accepted medical evidence. Not FDA evaluated. Do not use if allergic to any ingredient. Consult a doctor before use for serious conditions or if conditions worsen or persist. If pregnant or nursing, consult a doctor before use. Avoid contact with eyes. Do not use if safety seal is broken
or missing.

QUESTIONS

Questions? Call 866.642.2858 Made with care by Uriel, East Troy, WI 53120 www.urielpharmacy.com